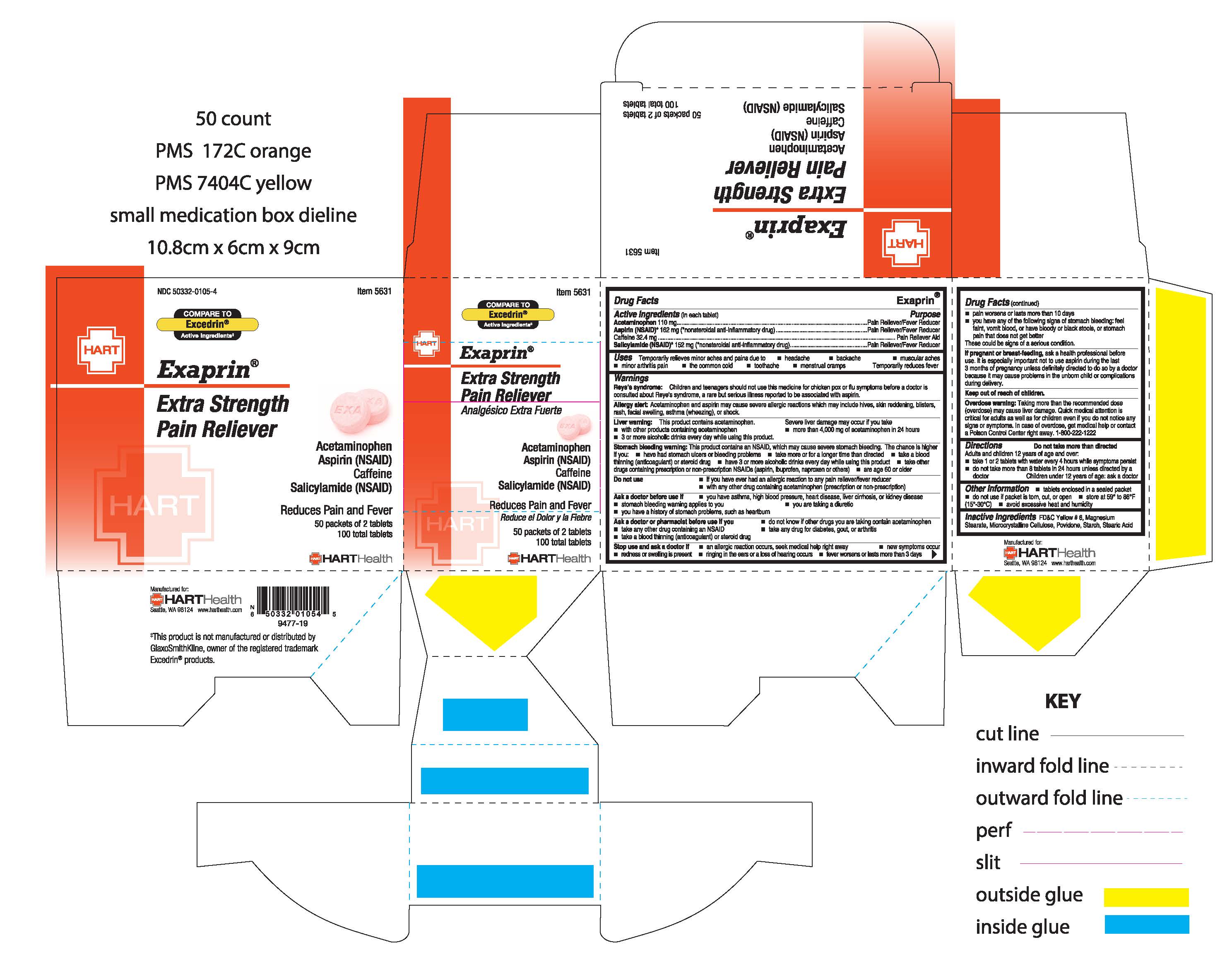 DRUG LABEL: EXAPRIN
NDC: 50332-0105 | Form: TABLET
Manufacturer: HART Health
Category: otc | Type: HUMAN OTC DRUG LABEL
Date: 20191130

ACTIVE INGREDIENTS: ACETAMINOPHEN 110 mg/1 1; ASPIRIN 162 mg/1 1; CAFFEINE 32.4 mg/1 1; SALICYLAMIDE 152 mg/1 1
INACTIVE INGREDIENTS: STARCH, CORN; FD&C YELLOW NO. 6; MAGNESIUM STEARATE; CELLULOSE, MICROCRYSTALLINE; POVIDONE; STEARIC ACID

EXAPRIN

Active Ingredients (in each tablet):

Acetaminophen 110mg

Aspirin (NSAID*) 162mg (*nonsteroidal anti-inflammatory drug)

Caffeine 32.4mg

Salicylamide (NSAID)* 152mg (*nonsteroidal anti-inflammatory drug)

Purpose:

Pain Reliever / Fever Reducer

Pain Reliever / Fever Reducer

Pain Reliever Aid

Pain Reliever / Fever Reducer

Uses:

Temporarily relieves minor aches and pains due to

- headache
- backache
- muscular aches
- minor arthritis pain
- the common cold
- toothache
- menstrual cramps

Temporarily reduces fever

Warnings:

Reye's syndrome: Children and teenagers should not use this medicine for chicken pox or flu symptoms before a doctor is consulted about Reye's syndrome, a rare but serious illness reported to be associated with aspirin.

Allergy alert: Acetaminophen and aspirin may cause severe allergic reactions which may include hives, skin reddening, blisters, rash, facial swelling, asthma (wheezing), or shock

Liver warning: This product contains acetaminophen. Severe liver damage may occur if you take

- more than 4,000 mg of acetaminophen in 24 hours
- with other products containing acetaminophen
- 3 more more alcoholic drinks every day while using this product

Stomach bleeding warning:

This product contains an NSAID, which may cause severe stomach bleeding. The chance is higher if you:

- are age 60 or older
- have had stomach ulcers or bleeding problems
- take more or for a longer time than directed
- take a blood thinning (anticoagulant) or steroid drug
- have 3 or more alcohol drinks every day while using this product
- take other drugs containing prescription or non-prescription NSAIDS (aspirin, ibuprofen, naproxen, others)

Do not use

- with any other drug containing acetaminophen (prescription or non-prescription)
- if you have ever had an allergic reaction to aspirin or any other pain reliever/fever reducer

Ask a doctor before use if

- stomach bleeding warning applies to you
- you have asthma, high blood pressure, heart disease, liver cirrhosis, or kidney disease
- you are taking a diuretic
- you have a history of stomach problems, such as heartburn

Ask a doctor or pharmacist before use if you

- take any other drug containing an NSAID
- take a blood thinning (anticoagulant) or steroid drug
- take any drug for diabetes, gout, or arthritis
- do not know if other drugs you are taking contain acetaminophen

Stop use and ask a doctor if

- an allergic reaction occurs, seek medical help right away
- new symptoms occur
- fever worsens or lasts more than 3 days
- pain worsens or lasts more than 10 days
- redness or swelling is present
- ringing in the ears or a loss of hearing occurs
- you have any of the following signs of stomach bleeding: feel faint, vomit blood, or have bloody or black stools, or stomach pain that does not get better

These could be signs of a serious condition

PREGNANCY OR BREAST FEEDING

If pregnant or breast-feeding, ask a health professional before use. It is especially important not to use aspirin during the last 3 months of pregnancy unless definitely directed to do so by a doctor because is may cause problems in the unborn child or complications during delivery

Keep out of reach of children

OVERDOSAGE

Overdose warning: Taking more than the recommended dose (overdose) may cause liver damage. Quick medical attention is critical for adults as well as for children even if you do not notice any signs or symptoms. In case of overdose, get medical help or contact a Poison Control Center right away. 1-800-222-1222

Directions:

do not take more than directed.

Adults and children 12 years of age and over:

- take 1 or 2 tablets with water every 4 hours while sympotms persist
- do not take more than 8 tablets in 24 hours unless directed by a doctor

Children under 12 years of age: ask a doctor

Inactive Ingredients:

FD&C Yellow #6, Magnesium Stearate, Microcrystalline Cellulose, Povidone, Starch, Stearic Acid